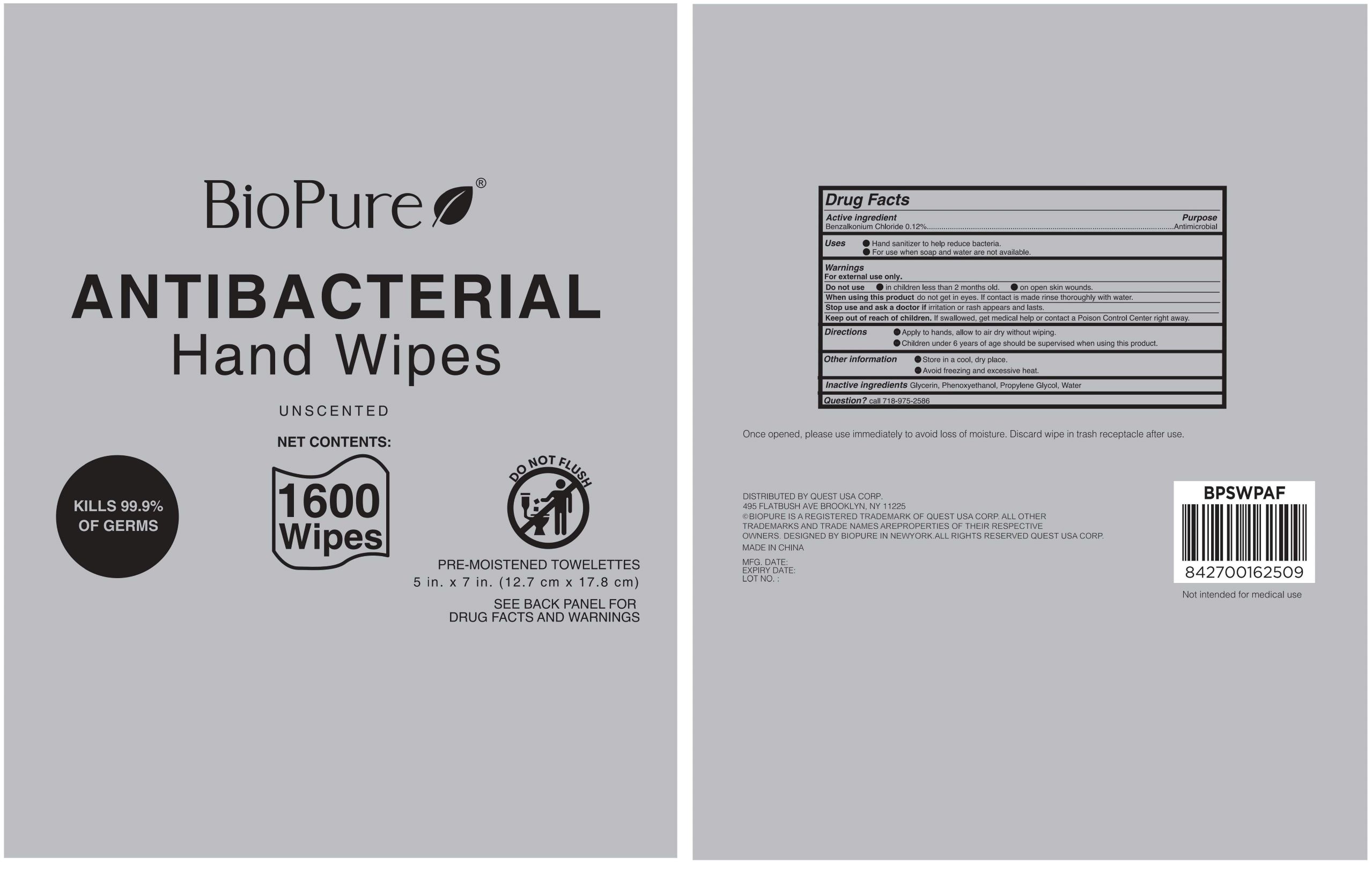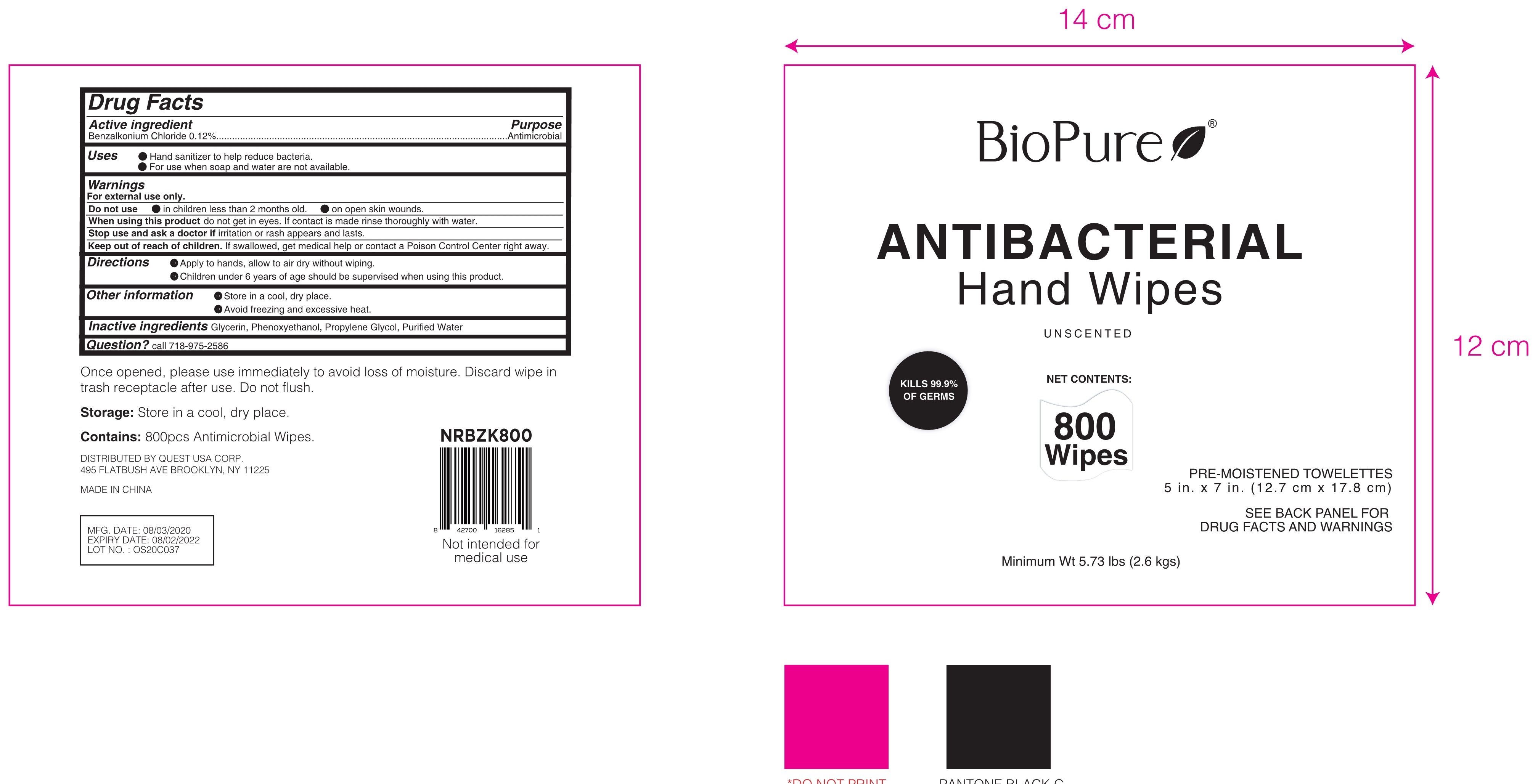 DRUG LABEL: Antibacterial Hand Wipes
NDC: 79866-005 | Form: CLOTH
Manufacturer: Osike Cosmetics Co., Ltd.
Category: otc | Type: HUMAN OTC DRUG LABEL
Date: 20221129

ACTIVE INGREDIENTS: BENZALKONIUM CHLORIDE 0.12 g/100 1
INACTIVE INGREDIENTS: PROPYLENE GLYCOL; PHENOXYETHANOL; WATER; GLYCERIN

79866-005
Antibacterial Hand Wipes

Active Ingredient(s)

Benzalkonium Chloride 0.12%

Purpose

Antimicroblal

Use

●Hand sanitizer to help reduce bacteria
●For use when soap and water are not available.

Warnings

For external use only.

Do not use

●on children less than 2 months old.
●on open skin wounds

When using this product do not get in eyes. If

contact is made rinse thoroughly with water.

Stop use and ask a doctor if irritation or rash appears and lasts.

Keep out of reach of children. If swallowed. get medical help or Contact a Poison Control Center right away.

Directions

●Apply to hands, allow to air dry without wiping.
●Children under 6 years of age should be supervised when using this product

Other information

●Store in a cool,dry place.
●Avoid freezing and excessive heat.

Inactive ingredients

Glycerin, Phenoxyethanol, Propylene Glycol, Water